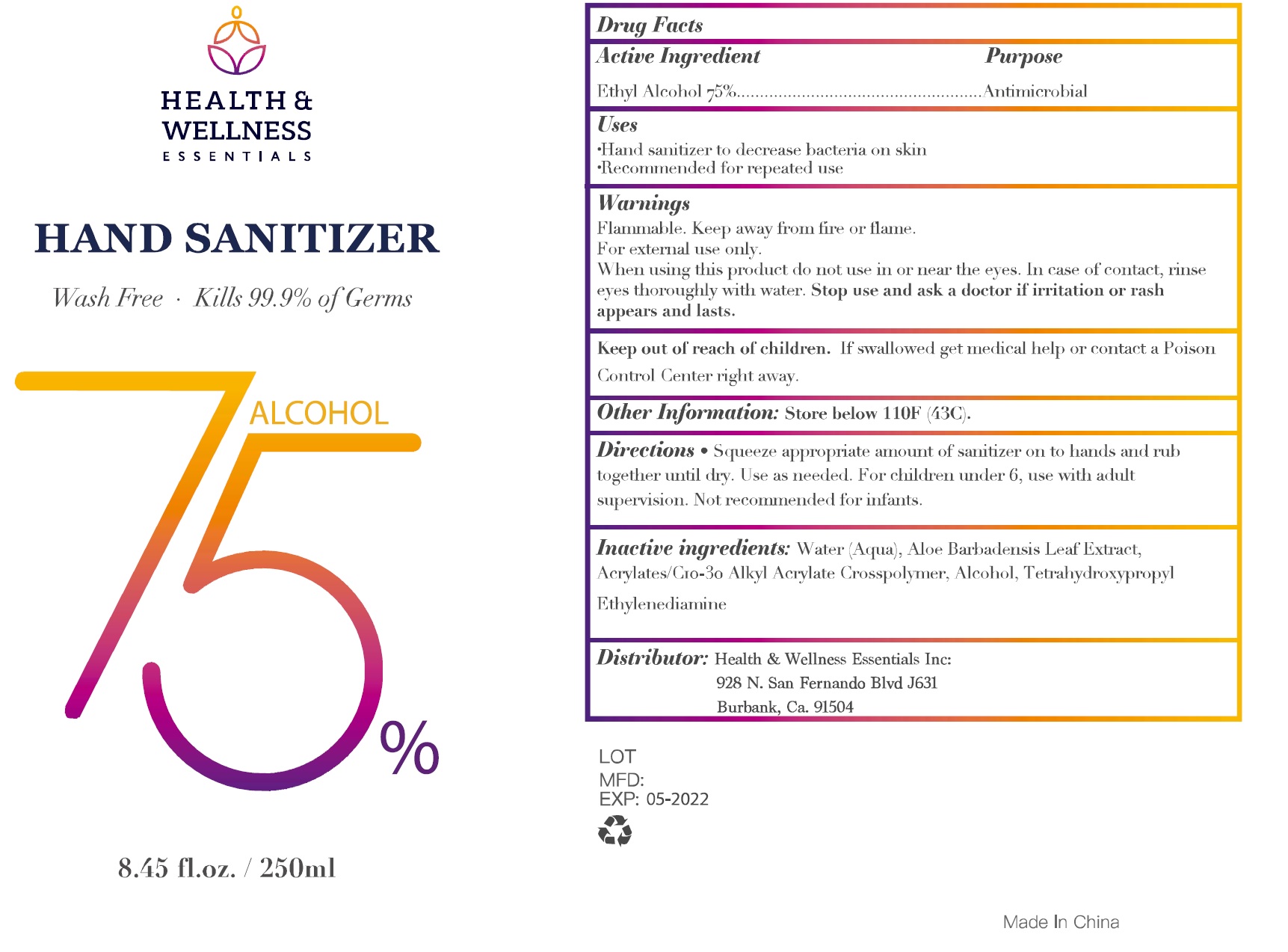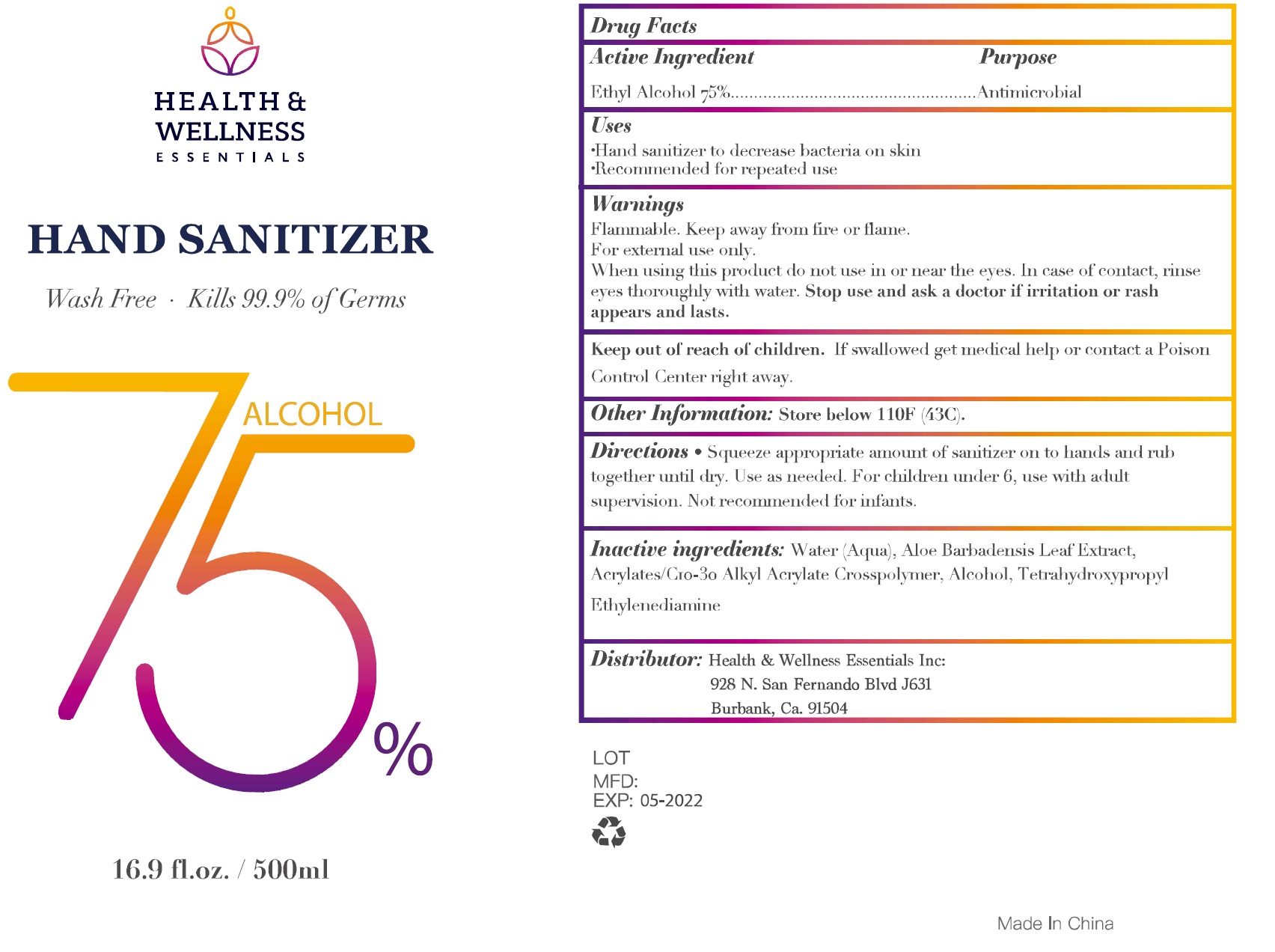 DRUG LABEL: Health and Wellness Essentials Hand Sanitizer
NDC: 78841-000 | Form: GEL
Manufacturer: Health & Wellness Essentials Inc.
Category: otc | Type: HUMAN OTC DRUG LABEL
Date: 20200629

ACTIVE INGREDIENTS: ALCOHOL 0.75 mL/1 mL
INACTIVE INGREDIENTS: WATER; ALOE VERA LEAF; CARBOMER INTERPOLYMER TYPE A (ALLYL SUCROSE CROSSLINKED); EDETOL

Health & Wellness Essentials Hand Sanitizer

Active Ingredient

Ethyl Alcohol 75%

Purpose

Antimicrobial

Uses

- Hand sanitizer to decrease bacteria on skin
- Recommended for repeated use

Warnings

Flammable. Keep away from fire or flame.

For external use only.

When using this product

do not use in or near the eyes. In case of contact, rinse eyes thoroughly with water.

Stop use and ask a doctor

if irritation or rash appears and lasts.

Keep out of reach of children.

If swallowed get medical help or contact a Poison Control Center right away.

Other Information:

Store below 110F (43C).

Directions

- Squeeze appropriate amount of sanitizer on to hands and rub together until dry. Use as needed. For children under 6, use with adult supervision. Not recommended for infants.

Inactive ingredients:

Water (Aqua), Aloe Barbadensis Leaf Extract, Acrylates/C10-30 Alkyl Acrylate Crosspolymer, Alcohol, Tetrahydroxypropyl Ethylenediamine